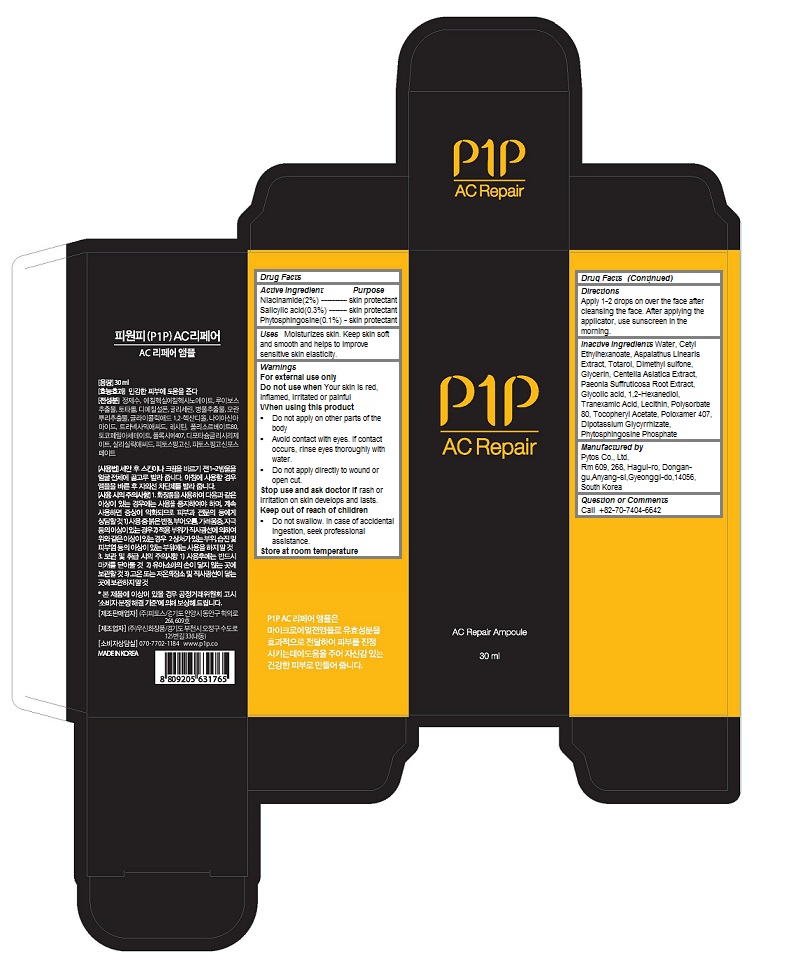 DRUG LABEL: P1P AC Repair Ampoule
NDC: 69579-108 | Form: LIQUID
Manufacturer: Phytos Co., Ltd.
Category: otc | Type: HUMAN OTC DRUG LABEL
Date: 20160107

ACTIVE INGREDIENTS: NIACINAMIDE 0.02 1/30 mL; Salicylic acid 0.003 1/30 mL; Phytosphingosine 0.001 1/30 mL
INACTIVE INGREDIENTS: water; Cetyl Ethylhexanoate; Totarol; Dimethyl sulfone; Glycerin; CENTELLA ASIATICA; PAEONIA SUFFRUTICOSA ROOT; Glycolic acid; 1,2-Hexanediol; Tranexamic Acid; EGG PHOSPHOLIPIDS; Polysorbate 80; .ALPHA.-TOCOPHEROL ACETATE; Poloxamer 407; GLYCYRRHIZINATE DIPOTASSIUM

P1P AC Repair Ampoule